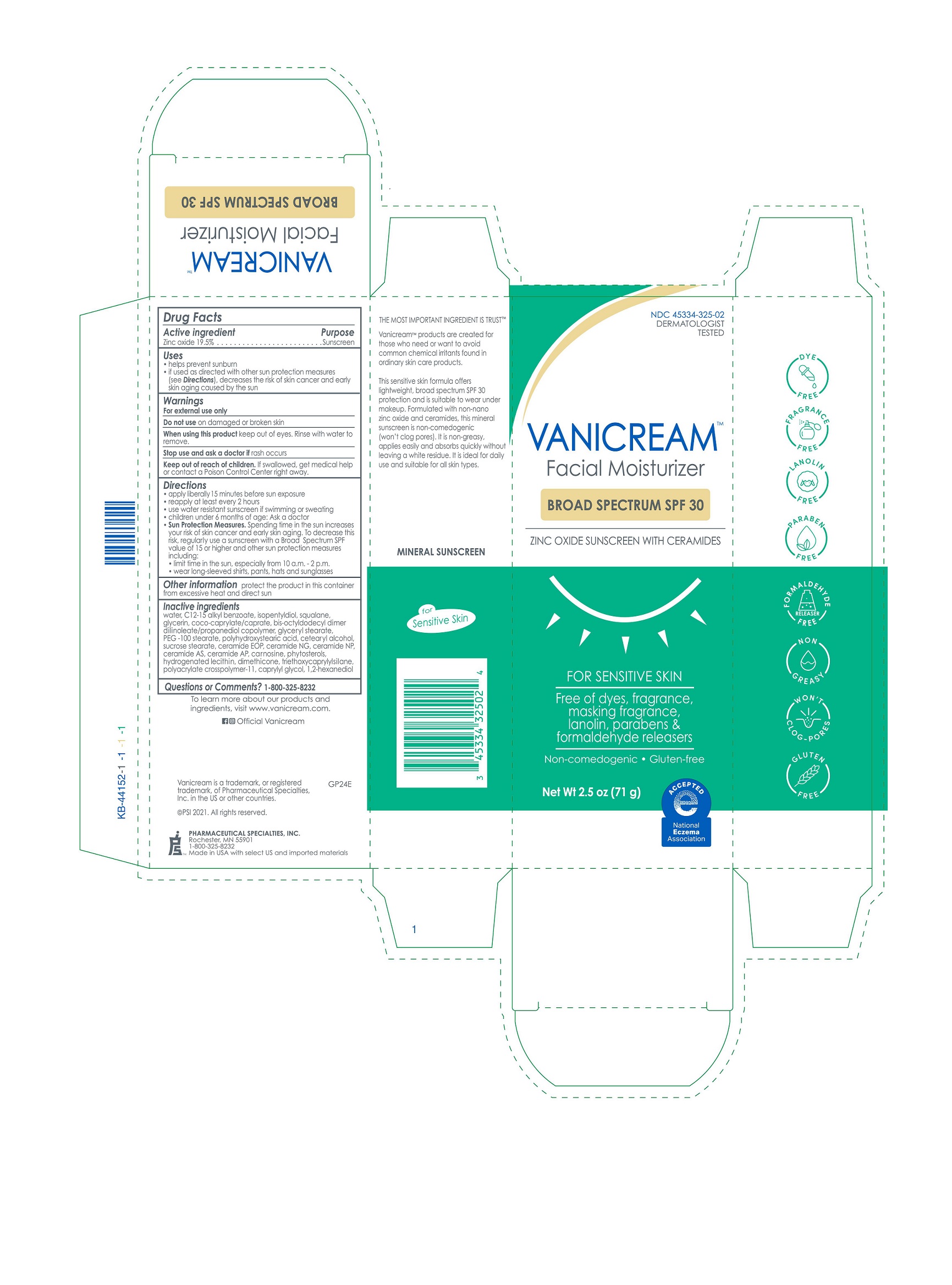 DRUG LABEL: Vanicream Facial Moisturizer Broad Spectrum SPF30
NDC: 45334-325 | Form: CREAM
Manufacturer: Pharmaceutical Specialties Inc
Category: otc | Type: HUMAN OTC DRUG LABEL
Date: 20241015

ACTIVE INGREDIENTS: ZINC OXIDE 19.5 g/100 g
INACTIVE INGREDIENTS: CARNOSINE; SOY STEROL; HYDROGENATED SOYBEAN LECITHIN; CERAMIDE NP; CERAMIDE 5; DIMETHICONE; CAPRYLYL GLYCOL; GLYCERYL 1-STEARATE; PEG-100 STEARATE; POLYHYDROXYSTEARIC ACID (2300 MW); ISOPENTYLDIOL; CETOSTEARYL ALCOHOL; ALKYL (C12-15) BENZOATE; WATER; SQUALANE; GLYCERIN; CERAMIDE NG; TRIETHOXYCAPRYLYLSILANE; AMMONIUM ACRYLOYL DIMETHYLTAURATE/METHACRYLATE, DIMETHYLACRYLAMIDE AND METHACRYLIC ACID COPOLYMER, PPG-3 GLYCERYL TRIACRYLATE CROSSLINKED (100000 MW); 1,2-HEXANEDIOL; COCOYL CAPRYLOCAPRATE; BIS-OCTYLDODECYL DIMER DILINOLEATE/PROPANEDIOL COPOLYMER; SUCROSE STEARATE; CERAMIDE 1; CERAMIDE AP

Vanicream Facial Moisturizer Broad Spectrum SPF30

Drug Facts

Active ingredient

Zinc oxide 19.5%

Purpose

Sunscreen

Uses

- helps prevent sunburn
- if used as directed with other sun protection measures (see Directions), decreases the risk of skin cancer and early skin aging caused by the sun

Warnings

For external use only

Do not use on damaged or broken skin

When using this product keep out of eyes. Rinse with water to remove.

Stop use and ask a doctor if rash occurs

Keep out of reach of children. If swallowed, get medical help or contact a Poison Control Center right away.

Directions

- apply liberally 15 minutes before sun exposure
- reapply at least every 2 hours
- use water resistant sunscreen if swimming or sweating
- children under 6 months of age: Ask a doctor
- Sun Protection Measures. Spending time in the sun increases your risk of skin cancer and early skin aging. To decrease this risk, regularly use a sunscreen with a Broad Spectrum SPF value of 15 or higher and other sun protection measures including:
- limit time in the sun, especially from 10 a.m. - 2 p.m.
- wear long-sleeved shirts, pants, hats and sunglasses

Other information

protect the product in this container from excessive heat and direct sun

INACTIVE INGREDIENT

Inactive ingredients water, C12-15 alkyl benzoate, isopentyldiol, squalane, glycerin, coco-caprylate/caprate, bis-octyldodecyl dimer dilinoleate/propanediol copolymer, glyceryl stearate, PEG-100 stearate, polyhydroxystearic acid, cetearyl alcohol, sucrose stearate, ceramide EOP, ceramide NG, ceramide NP, ceramide AS, ceramide AP, carnosine, phytosterols, hydrogenated lecithin, dimethicone, triethoxycaprylylsilane, polyacrylate crosspolymer-11, caprylyl glycol, 1,2-hexanediol

Questions or Comments? 1-800-325-8232

PACKAGE LABEL

NDC 45334-325-02

DERMATOLOGIST TESTED

VANICREAM™ Facial Moisturizer

BROAD SPECTRUM SPF 30

ZINC OXIDE SUNSCREEN WITH CERAMIDES

FOR SENSITIVE SKIN

Free of dyes, fragrance, masking fragrance, lanolin, parabens & formaldehyde releasers

Non-comedogenic

Gluten-free

Net Wt 2.5 oz (71 g)

PHARMACEUTICAL SPECIALTIES, INC.

ROCHESTER, MN 55901

1-800-325-8232

Made in USA with select US and imported materials